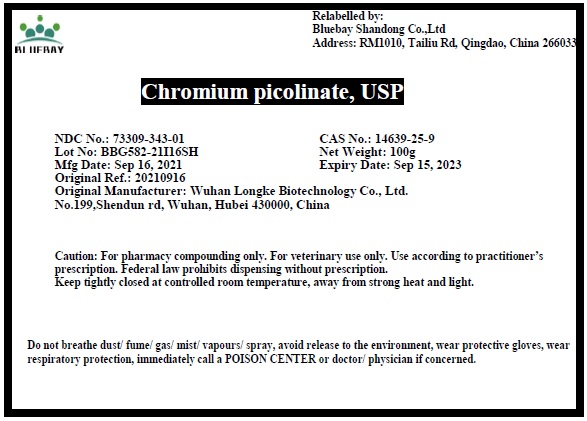 DRUG LABEL: Chromium picolinate
NDC: 73309-343 | Form: POWDER
Manufacturer: BLUEBAY SHANDONG CO.,LTD
Category: other | Type: BULK INGREDIENT
Date: 20211104

ACTIVE INGREDIENTS: CHROMIUM PICOLINATE 1 g/1 g

Chromium picolinate